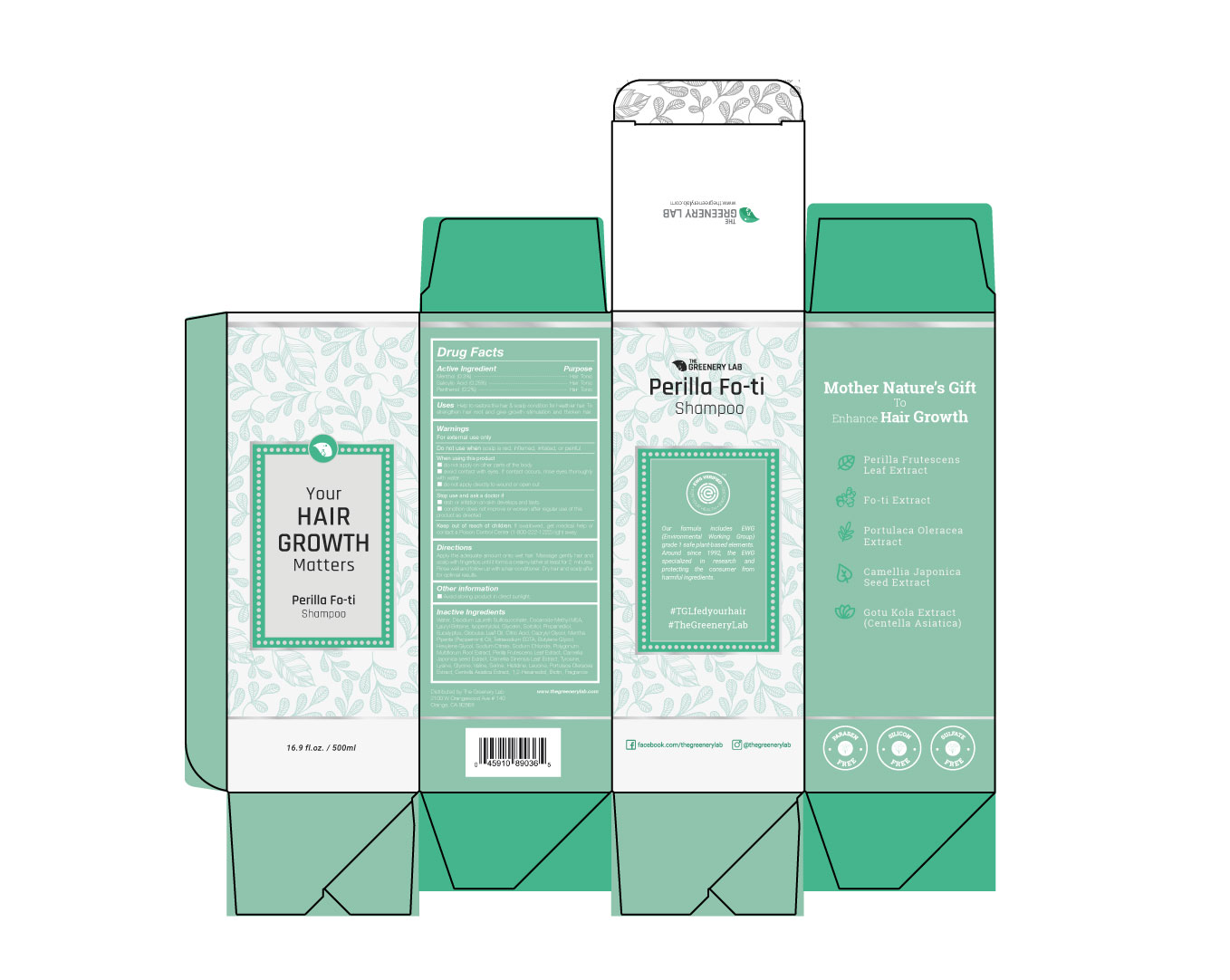 DRUG LABEL: Perilla Fo ti
NDC: 72636-100 | Form: SHAMPOO
Manufacturer: The Greenery Lab
Category: otc | Type: HUMAN OTC DRUG LABEL
Date: 20181114

ACTIVE INGREDIENTS: PANTHENOL 1 g/500 g; MENTHOL 1.5 g/500 g; SALICYLIC ACID 1.25 g/500 g
INACTIVE INGREDIENTS: WATER

Perilla Fo-ti Shampoo

Directions

Apply the adequate amount onto wet hair. Massage gently hair and scalp with fingertips until it forms a creamy lather at least for 2 minutes. Rinse well and follow up with a hair conditioner.

Dry hair and scalp after for optimal results

Warnings

For external use only

Do not use when scalp is red, inflamed, irritated, or painful

When using this product

do not apply on other parts of the body

avoid contact with eyes. If contact occurs, rinse eyes thoroughly with water

do not apply directly to wound or open cut

Stop use and ask a doctor if

rash or irritation on skin develops and lasts

condition does not improve or worsen after regular use of this product as directed

Inactive Ingredients

Water, Disodium Laureth Sulfosuccinate, Cocamide Methyl MEA, Lauryl Betaine, Isopentyldiol, Glycerin, Sorbitol, Propanediol, Eucalyptus, Globulus Leaf Oil, Citric Acid, Caprylyl Glycol, Mentha Piperita (Peppermint) Oil, Tetrasodium EDTA, Butylene Glycol, Hexylene Glycol, Sodium Citrate, Sodium Chloride, Polygonum Multiflorum Root Extract, Perilla Frutescens Leaf Extract, Camellia Japonica seed Extract, Camellia Sinensis Leaf Extract, Tyrosine, Lysine, Glycine, Valine, Serine, Histidine, Leucine, Portulaca Oleracea Extract, Centella Asiatica Extract, 1,2-Hexanediol, Biotin, Fragrance

Uses

Help to restore the hair & scalp condition for healthier hair. To strengthen hair root and give growth stimulation and thicken hair.

Keep out of reach of children

If swallowed, get medical help or contact a Poison Control Center (1-800-222-1222) right away.

Purpose

Hair Tonic

Active Ingredient

Menthol (0.3%)

Salicylic Acid (0.25%)

Panthenol (0.2%)